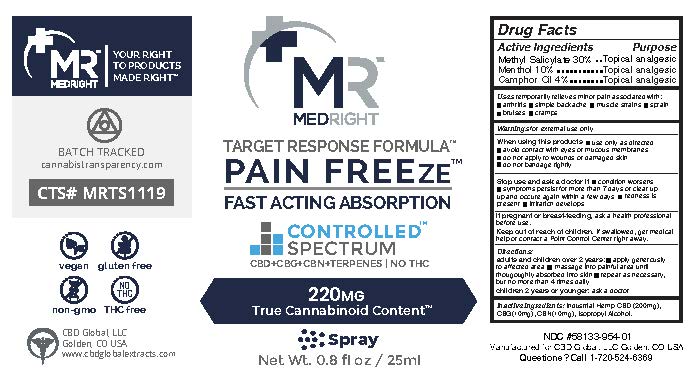 DRUG LABEL: CBD Global Freeze
NDC: 58133-954 | Form: SPRAY
Manufacturer: Cosmetic Specialty Labs, Inc.
Category: otc | Type: HUMAN OTC DRUG LABEL
Date: 20220928

ACTIVE INGREDIENTS: MENTHOL 10 g/100 mL; METHYL SALICYLATE 30 g/100 mL; CAMPHOR (SYNTHETIC) 4 g/100 mL
INACTIVE INGREDIENTS: CANNABIDIOL; ISOPROPYL ALCOHOL; CANNABINOL; CANNABIGEROL

Active Incredients

Methyl Salicylate 30%

Menthol 10%

Camphor Oil 4%

Purpose

Topical analgesi

Uses

temporarily relieves minor pain associated with: • arthritis • simple backache • muscle strains • sprains • bruises • cramps

Warnings

for external use only

WHEN USING

When using this prodcut• use only as directed • avoid contact with eyes or mucous membranes • do not apply to wounds or damaged skin •do not bandage tightly

Stop use and ask a doctor if• condition worsens • symptoms persist for more than 7 days or clear up and occur again within a few days • redness is present • irritation develeps

KEEP OUT OF REACH OF CHILDREN

If pregnant or breast-feeding, ask a health professional before use.

Keep out of reach of children. If swallowed, get medical help or contact Poison Control Center right away.

Directions:

Adults and children over 2 years:• apply generously to affected area • massage into painful area until throughly absorbed into skin • repeat as necessary, but no more than 4 time daily

Children 2 years or younger: ask a doctor

Inactive ingredients

Industrial Hemp CBD(200mg), CBG(10mg), CBN(10mg), Isopropyl Alcohol

RECENT MAJOR CHANGES

updated effective date to 09-28-2022 and updated the Secion Type